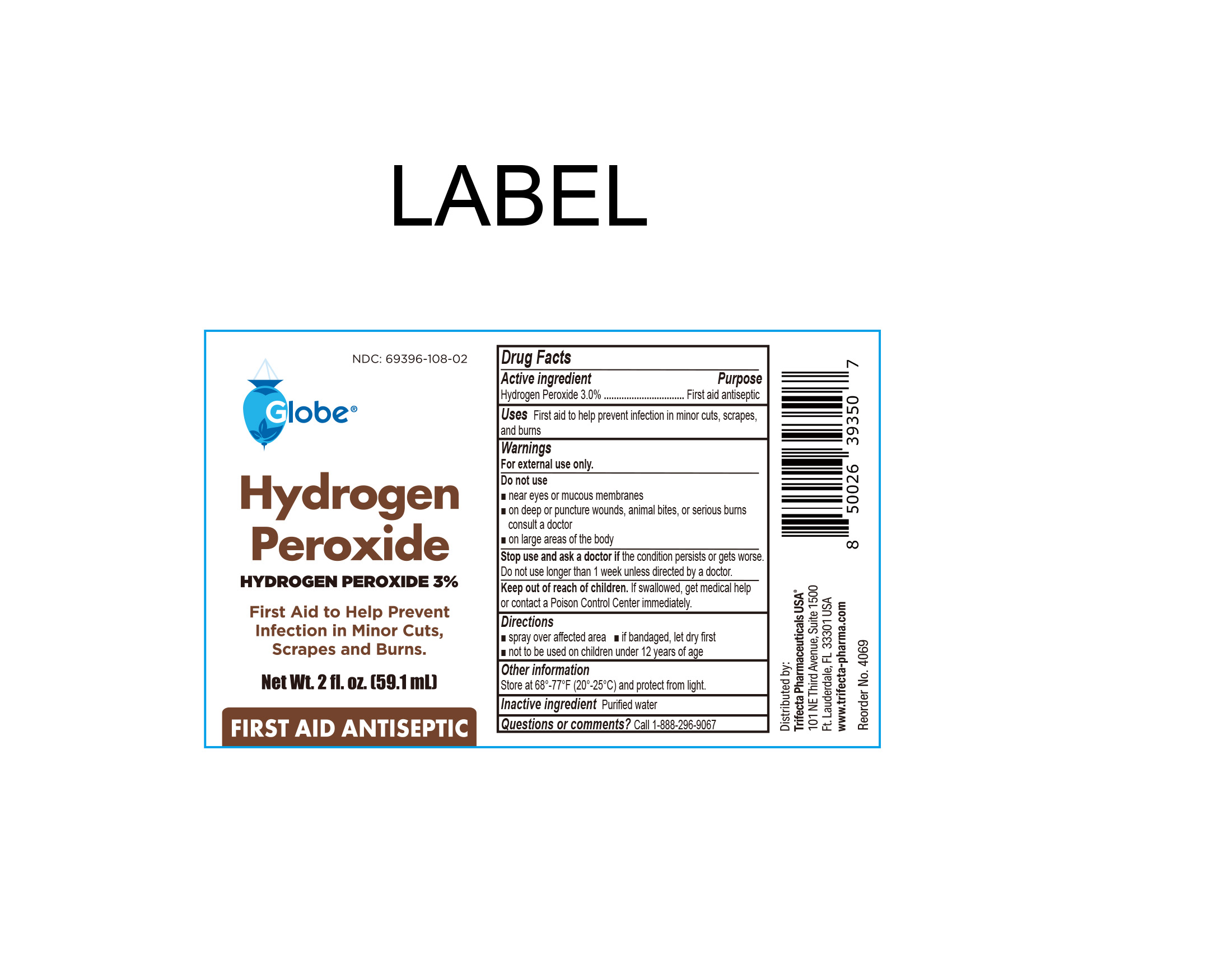 DRUG LABEL: Hydrogen Peroxide
NDC: 69396-108 | Form: SPRAY
Manufacturer: Trifecta Pharmaceuticals USA, LLC.
Category: otc | Type: HUMAN OTC DRUG LABEL
Date: 20240102

ACTIVE INGREDIENTS: HYDROGEN PEROXIDE 30 mL/1 L
INACTIVE INGREDIENTS: WATER

Hydrogen Peroxide

Active Ingredient

Hydrogen Peroxide 3.0%

Purpose

First Aid Antiseptic

INDICATIONS AND USAGE

First Aid to help prevent infection in minor cuts, scrapes, and burns.

Warnings

For External Use Only

Stop use and ask a doctor

- If the condition persists or gets worse. Do not use longer than 1 week unlesss directed by a doctor.

Keep out of the reach of children

If swallowed, get medical help or contact a Poison Control Center immediately

Directions

- Spray over affected area
- If bandaged, let dry first
- Not to be used on children under 12 years of age

Other information

- Store at controlled room temperature 68º-77ºF (20º-25ºC)

Inactive Ingredients

Water

Questions or Comments

Call 1-888-296-9067

Distributed By:

Trifecta Pharmaceuticals USA, LLC.

101 NE Third Avenue, Suite 1500

Ft. Lauderdale, FL. 33301 USA

www.trifecta-pharma.com

SKU: 4069-FBA

Made in China